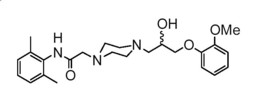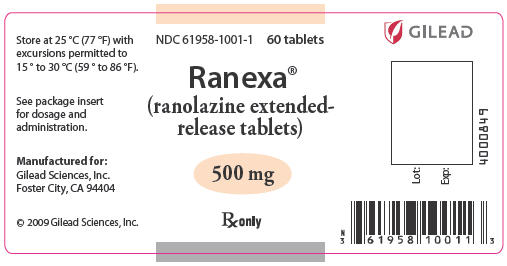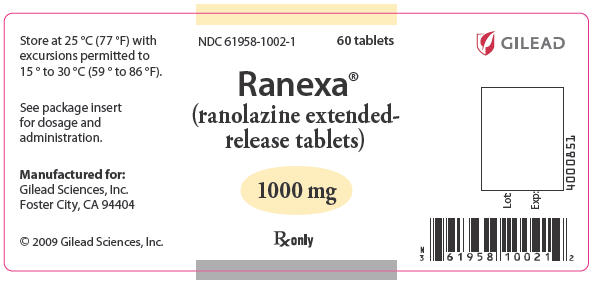 DRUG LABEL: Ranexa
NDC: 61958-1001 | Form: TABLET, FILM COATED, EXTENDED RELEASE
Manufacturer: Gilead Sciences, Inc.
Category: prescription | Type: HUMAN PRESCRIPTION DRUG LABEL
Date: 20100426

ACTIVE INGREDIENTS: ranolazine 500 mg/1 1
INACTIVE INGREDIENTS: carnauba wax; HYPROMELLOSE 2910 (5 CPS); magnesium stearate; METHACRYLIC ACID - ETHYL ACRYLATE COPOLYMER (1:1) TYPE A; CELLULOSE, MICROCRYSTALLINE; sodium hydroxide; polyethylene glycol 400; titanium dioxide; polysorbate 80; FD&C Yellow No. 6; Aluminum Oxide; hypromellose 2910 (3 cps); hypromellose 2910 (6 cps)

HIGHLIGHTS OF PRESCRIBING INFORMATION

These highlights do not include all the information needed to use
Ranexa safely and effectively. See full prescribing information for
Ranexa.
Ranexa (ranolazine) extended-release tablets
Initial U.S. Approval: 2006

RECENT MAJOR CHANGES

Indications and Usage (1) | 11/2008
Contraindications (4) | 11/2008

1 INDICATIONS AND USAGE

Ranexa is indicated for the treatment of chronic angina. (1)

2 DOSAGE AND ADMINISTRATION

500 mg twice daily and increase to 1000 mg twice daily, based on clinical symptoms (2.1)

3 DOSAGE FORMS AND STRENGTHS

Extended-release tablets: 500 mg, 1000 mg (3)

4 CONTRAINDICATIONS

- Use with strong CYP3A inhibitors (e.g., ketoconazole, clarithromycin, nelfinavir) (4, 7.1)
- Use with CYP3A inducers (e.g., rifampin, phenobarbital) (4, 7.1)
- Use in patients with clinically significant hepatic impairment (4, 8.6)

5 WARNINGS AND PRECAUTIONS

- QT interval prolongation: Can occur with ranolazine. Little data available on high doses, long exposure, use with QT interval-prolonging drugs, or potassium channel variants causing prolonged QT interval. (5.1)

6 ADVERSE REACTIONS

Most common adverse reactions (> 4% and more common than with placebo) are dizziness, headache, constipation, nausea. (6.1)

To report SUSPECTED ADVERSE REACTIONS, contact Gilead Sciences, Inc., at 1-800-GILEAD-5 or FDA at 1-800-FDA-1088 or www.fda.gov/medwatch.

7 DRUG INTERACTIONS

- CYP3A inhibitors: Do not use Ranexa with strong CYP3A inhibitors. With moderate 3A inhibitors (e.g., diltiazem, verapamil, erythromycin), limit maximum dose of Ranexa to 500 mg twice daily. (7.1)
- CYP3A inducers: Do not use Ranexa with CYP3A inducers. (7.1)
- P-gp inhibitors (e.g., cyclosporine): May need to lower Ranexa dose based on clinical response. (7.1)
- Drugs transported by P-gp or metabolized by CYP2D6 (e.g., digoxin, tricyclic antidepressants): May need reduced doses of these drugs when used with Ranexa. (7.2)

FULL PRESCRIBING INFORMATION

1 INDICATIONS AND USAGE

Ranexa is indicated for the treatment of chronic angina.

Ranexa may be used with beta-blockers, nitrates, calcium channel blockers, anti-platelet therapy, lipid-lowering therapy, ACE inhibitors, and angiotensin receptor blockers.

2 DOSAGE AND ADMINISTRATION

2.1 Dosing Information

Initiate Ranexa dosing at 500 mg twice daily and increase to 1000 mg twice daily, as needed, based on clinical symptoms. Take Ranexa with or without meals. Swallow Ranexa tablets whole; do not crush, break, or chew.

The maximum recommended daily dose of Ranexa is 1000 mg twice daily.

If a dose of Ranexa is missed, take the prescribed dose at the next scheduled time; do not double the next dose.

2.2 Dose Modification

Dose adjustments may be needed when Ranexa is taken in combination with certain other drugs [see Drug Interactions (7.1)]. Limit the maximum dose of Ranexa to 500 mg twice daily in patients on diltiazem, verapamil, and other moderate CYP3A inhibitors. Down-titrate Ranexa based on clinical response in patients concomitantly treated with P-gp inhibitors, such as cyclosporine.

3 DOSAGE FORMS AND STRENGTHS

Ranexa is supplied as film-coated, oblong-shaped, extended-release tablets in the following strengths:

- 500 mg tablets are light orange, with CVT500 on one side
- 1000 mg tablets are pale yellow, with CVT1000 on one side

4 CONTRAINDICATIONS

Ranexa is contraindicated in patients:

- Taking strong inhibitors of CYP3A [see Drug Interactions (7.1)]
- Taking inducers of CYP3A [see Drug Interactions (7.1)]
- With clinically significant hepatic impairment [see Use in Specific Populations (8.6)]

5 WARNINGS AND PRECAUTIONS

5.1 QT Interval Prolongation

Ranolazine blocks IKr and prolongs the QTc interval in a dose-related manner.

Clinical experience in an acute coronary syndrome population did not show an increased risk of proarrhythmia or sudden death [see Clinical Studies (14.2)]. However, there is little experience with high doses (> 1000 mg twice daily) or exposure, other QT-prolonging drugs, or potassium channel variants resulting in a long QT interval.

6 ADVERSE REACTIONS

6.1 Clinical Trial Experience

Because clinical trials are conducted under widely varying conditions, adverse reaction rates observed in the clinical trials of a drug cannot be directly compared to rates in the clinical trials of another drug and may not reflect the rates observed in practice.

A total of 2,018 patients with chronic angina were treated with ranolazine in controlled clinical trials. Of the patients treated with Ranexa, 1,026 were enrolled in three double-blind, placebo-controlled, randomized studies (CARISA, ERICA, MARISA) of up to 12 weeks duration. In addition, upon study completion, 1,251 patients received treatment with Ranexa in open-label, long-term studies; 1,227 patients were exposed to Ranexa for more than 1 year, 613 patients for more than 2 years, 531 patients for more than 3 years, and 326 patients for more than 4 years.

At recommended doses, about 6% of patients discontinued treatment with Ranexa because of an adverse event in controlled studies in angina patients compared to about 3% on placebo. The most common adverse events that led to discontinuation more frequently on Ranexa than placebo were dizziness (1.3% versus 0.1%), nausea (1% versus 0%), asthenia, constipation, and headache (each about 0.5% versus 0%). Doses above 1000 mg twice daily are poorly tolerated.

In controlled clinical trials of angina patients, the most frequently reported treatment-emergent adverse reactions (> 4% and more common on Ranexa than on placebo) were dizziness (6.2%), headache (5.5%), constipation (4.5%), and nausea (4.4%). Dizziness may be dose-related. In open-label, long-term treatment studies, a similar adverse reaction profile was observed.

The following additional adverse reactions occurred at an incidence of 0.5 to 2.0% in patients treated with Ranexa and were more frequent than the incidence observed in placebo-treated patients:

Cardiac Disorders – bradycardia, palpitations

Ear and Labyrinth Disorders – tinnitus, vertigo

Gastrointestinal Disorders – abdominal pain, dry mouth, vomiting

General Disorders and Administrative Site Adverse Events – peripheral edema

Respiratory, Thoracic, and Mediastinal Disorders – dyspnea

Vascular Disorders – hypotension, orthostatic hypotension

Other (< 0.5%) but potentially medically important adverse reactions observed more frequently with Ranexa than placebo treatment in all controlled studies included: angioedema, renal failure, eosinophilia, blurred vision, confusional state, hematuria, hypoesthesia, paresthesia, tremor, pulmonary fibrosis, thrombocytopenia, leukopenia, and pancytopenia.

A large clinical trial in acute coronary syndrome patients was unsuccessful in demonstrating a benefit for Ranexa, but there was no apparent proarrhythmic effect in these high-risk patients [see Clinical Trials (14.2)].

Laboratory Abnormalities

Ranexa produces small reductions in hemoglobin A1c. Ranexa is not a treatment for diabetes.

Ranexa produces elevations of serum creatinine by 0.1 mg/dL, regardless of previous renal function. The elevation has a rapid onset, shows no signs of progression during long-term therapy, is reversible after discontinuation of Ranexa, and is not accompanied by changes in BUN. In healthy volunteers, Ranexa 1000 mg twice daily had no effect upon the glomerular filtration rate. The elevated creatinine levels are likely due to a blockage of creatinine's tubular secretion by ranolazine or one of its metabolites.

7 DRUG INTERACTIONS

7.1 Effects of Other Drugs on Ranolazine

Ranolazine is primarily metabolized by CYP3A and is a substrate of P-glycoprotein (P-gp).

CYP3A Inhibitors

Do not use Ranexa with strong CYP3A inhibitors, including ketoconazole, itraconazole, clarithromycin, nefazodone, nelfinavir, ritonavir, indinavir, and saquinavir. Ketoconazole (200 mg twice daily) increases average steady-state plasma concentrations of ranolazine 3.2-fold [see Contraindications (4)].

Limit the dose of Ranexa to 500 mg twice daily in patients on moderate CYP3A inhibitors, including diltiazem, verapamil, aprepitant, erythromycin, fluconazole, and grapefruit juice or grapefruit-containing products. Diltiazem (180–360 mg daily) and verapamil (120 mg three times daily) increase ranolazine steady-state plasma concentrations about 2-fold [see Dosage and Administration (2.2)].

Weak CYP3A inhibitors such as simvastatin (20 mg once daily) and cimetidine (400 mg three times daily) do not increase the exposure to ranolazine in healthy volunteers.

P-gp Inhibitors

Down-titrate Ranexa based on clinical response in patients concomitantly treated with P-gp inhibitors, such as cyclosporine [see Dosage and Administration (2.2)].

CYP3A and P-gp Inducers

Avoid co-administration of Ranexa and CYP3A inducers such as rifampin, rifabutin, rifapentin, phenobarbital, phenytoin, carbamazepine, and St. John's wort. Rifampin (600 mg once daily) decreases the plasma concentration of ranolazine (1000 mg twice daily) by approximately 95% by induction of CYP3A and, probably, P-gp.

CYP2D6 Inhibitors

The potent CYP2D6 inhibitor, paroxetine (20 mg once daily), increases ranolazine concentrations 1.2-fold. No dose adjustment of Ranexa is required in patients treated with CYP2D6 inhibitors.

Digoxin

Digoxin (0.125 mg) does not significantly alter ranolazine levels.

7.2 Effects of Ranolazine on Other Drugs

In vitro studies indicate that ranolazine and its O-demethylated metabolite are weak inhibitors of CYP3A, moderate inhibitors of CYP2D6 and moderate P-gp inhibitors. Ranolazine and its most abundant metabolites are not known to inhibit the metabolism of substrates for CYP 1A2, 2C8, 2C9, 2C19, or 2E1 in human liver microsomes, suggesting that ranolazine is unlikely to alter the pharmacokinetics of drugs metabolized by these enzymes.

Drugs Metabolized by CYP3A

The plasma levels of simvastatin, a CYP3A substrate, and its active metabolite are each increased about 2-fold in healthy subjects receiving simvastatin (80 mg once daily) and Ranexa (1000 mg twice daily). Dose adjustments of simvastatin are not required when Ranexa is co-administered with simvastatin.

The pharmacokinetics of diltiazem is not affected by ranolazine in healthy volunteers receiving diltiazem 60 mg three times daily and Ranexa 1000 mg twice daily.

Drugs Transported by P-gp

Ranexa (1000 mg twice daily) causes a 1.5-fold elevation of digoxin plasma concentrations. The dose of digoxin may have to be adjusted.

Drugs Metabolized by CYP2D6

Ranolazine or its metabolites partially inhibit CYP2D6. There are no studies of concomitant use of Ranexa with other drugs metabolized by CYP2D6, such as tricyclic antidepressants and antipsychotics, but lower doses of CYP2D6 substrates may be required.

8 USE IN SPECIFIC POPULATIONS

8.1 Pregnancy

TERATOGENIC EFFECTS

Pregnancy Category C

In animal studies, ranolazine at exposures 1.5 (rabbit) to 2 (rat) times the usual human exposure caused maternal toxicity and misshapen sternebrae and reduced ossification in offspring. These doses in rats and rabbits were associated with an increased maternal mortality rate [see Reproductive Toxicology Studies (13.3)]. There are no adequate well-controlled studies in pregnant women. Ranexa should be used during pregnancy only when the potential benefit to the patient justifies the potential risk to the fetus.

8.3 Nursing Mothers

It is not known whether ranolazine is excreted in human milk. Because many drugs are excreted in human milk and because of the potential for serious adverse reactions from ranolazine in nursing infants, decide whether to discontinue nursing or to discontinue Ranexa, taking into account the importance of the drug to the mother.

8.4 Pediatric Use

Safety and effectiveness have not been established in pediatric patients.

8.5 Geriatric Use

Of the chronic angina patients treated with Ranexa in controlled studies, 496 (48%) were ≥ 65 years of age, and 114 (11%) were ≥ 75 years of age. No overall differences in efficacy were observed between older and younger patients. There were no differences in safety for patients ≥ 65 years compared to younger patients, but patients ≥ 75 years of age on ranolazine, compared to placebo, had a higher incidence of adverse events, serious adverse events, and drug discontinuations due to adverse events. In general, dose selection for an elderly patient should usually start at the low end of the dosing range, reflecting the greater frequency of decreased hepatic, renal, or cardiac function, and of concomitant disease, or other drug therapy.

8.6 Use in Patients with Hepatic Impairment

Ranexa is contraindicated in patients with clinically significant hepatic impairment. Plasma concentrations of ranolazine were increased by 30% in patients with mild (Child-Pugh Class A) and by 60% in patients with moderate (Child-Pugh Class B) hepatic impairment. This was not enough to account for the 3-fold increase in QT prolongation seen in patients with mild to severe hepatic impairment [see Contraindications (4)].

8.7 Use in Patients with Renal Impairment

In patients with varying degrees of renal impairment, ranolazine plasma levels increased up to 50%. The pharmacokinetics of ranolazine has not been assessed in patients on dialysis.

8.8 Use in Patients with Heart Failure

Heart failure (NYHA Class I to IV) had no significant effect on ranolazine pharmacokinetics. Ranexa had minimal effects on heart rate and blood pressure in patients with angina and heart failure NYHA Class I to IV. No dose adjustment of Ranexa is required in patients with heart failure.

8.9 Use in Patients with Diabetes Mellitus

A population pharmacokinetic evaluation of data from angina patients and healthy subjects showed no effect of diabetes on ranolazine pharmacokinetics. No dose adjustment is required in patients with diabetes.

Ranexa produces small reductions in HbA1c in patients with diabetes, the clinical significance of which is unknown. Ranexa should not be considered a treatment for diabetes.

10 OVERDOSAGE

High oral doses of ranolazine produce dose-related increases in dizziness, nausea, and vomiting. High intravenous exposure also produces diplopia, paresthesia, confusion, and syncope. In addition to general supportive measures, continuous ECG monitoring may be warranted in the event of overdose.

Since ranolazine is about 62% bound to plasma proteins, hemodialysis is unlikely to be effective in clearing ranolazine.

11 DESCRIPTION

Ranexa (ranolazine) is available as a film-coated, non-scored, extended-release tablet for oral administration.

Ranolazine is a racemic mixture, chemically described as 1-piperazineacetamide, N-(2,6-dimethylphenyl)-4-[2-hydroxy-3-(2-methoxyphenoxy)propyl]-, (±)-. It has an empirical formula of C24H33N3O4, a molecular weight of 427.54 g/mole, and the following structural formula:

Ranolazine is a white to off-white solid. Ranolazine is soluble in dichloromethane and methanol; sparingly soluble in tetrahydrofuran, ethanol, acetonitrile, and acetone; slightly soluble in ethyl acetate, isopropanol, toluene, and ethyl ether; and very slightly soluble in water.

Ranexa tablets contain 500 mg or 1000 mg of ranolazine and the following inactive ingredients: carnauba wax, hypromellose, magnesium stearate, methacrylic acid copolymer (Type C), microcrystalline cellulose, polyethylene glycol, sodium hydroxide, and titanium dioxide. Additional inactive ingredients for the 500 mg tablet include polysorbate 80 and FD&C Yellow No. 6 Lake; additional inactive ingredients for the 1000 mg tablet include lactose monohydrate, triacetin, and Iron Oxide Yellow.

12 CLINICAL PHARMACOLOGY

12.1 Mechanism of Action

The mechanism of action of ranolazine's antianginal effects has not been determined. Ranolazine has anti-ischemic and antianginal effects that do not depend upon reductions in heart rate or blood pressure. It does not affect the rate-pressure product, a measure of myocardial work, at maximal exercise. Ranolazine at therapeutic levels can inhibit the cardiac late sodium current (INa). However, the relationship of this inhibition to angina symptoms is uncertain.

The QT prolongation effect of ranolazine on the surface electrocardiogram is the result of inhibition of IKr, which prolongs the ventricular action potential.

12.2 Pharmacodynamics

Hemodynamic Effects

Patients with chronic angina treated with Ranexa in controlled clinical studies had minimal changes in mean heart rate (< 2 bpm) and systolic blood pressure (< 3 mm Hg). Similar results were observed in subgroups of patients with CHF NYHA Class I or II, diabetes, or reactive airway disease, and in elderly patients.

Electrocardiographic Effects

Dose and plasma concentration-related increases in the QTc interval [see Warnings and Precautions (5.1)], reductions in T wave amplitude, and, in some cases, notched T waves, have been observed in patients treated with Ranexa. These effects are believed to be caused by ranolazine and not by its metabolites. The relationship between the change in QTc and ranolazine plasma concentrations is linear, with a slope of about 2.6 msec/1000 ng/mL, through exposures corresponding to doses several-fold higher than the maximum recommended dose of 1000 mg twice daily. The variable blood levels attained after a given dose of ranolazine give a wide range of effects on QTc. At Tmax following repeat dosing at 1000 mg twice daily, the mean change in QTc is about 6 msec, but in the 5% of the population with the highest plasma concentrations, the prolongation of QTc is at least 15 msec. In subjects with mild or moderate hepatic impairment, the relationship between plasma level of ranolazine and QTc is much steeper [see Contraindications (4)].

Age, weight, gender, race, heart rate, congestive heart failure, diabetes, and renal impairment did not alter the slope of the QTc-concentration relationship of ranolazine.

No proarrhythmic effects were observed on 7-day Holter recordings in 3,162 acute coronary syndrome patients treated with Ranexa. There was a significantly lower incidence of arrhythmias (ventricular tachycardia, bradycardia, supraventricular tachycardia, and new atrial fibrillation) in patients treated with Ranexa (80%) versus placebo (87%), including ventricular tachycardia ≥ 3 beats (52% versus 61%). However, this difference in arrhythmias did not lead to a reduction in mortality, a reduction in arrhythmia hospitalization, or a reduction in arrhythmia symptoms.

12.3 Pharmacokinetics

Ranolazine is extensively metabolized in the gut and liver and its absorption is highly variable. For example, at a dose of 1000 mg twice daily, the mean steady-state Cmax was 2600 ng/mL with 95% confidence limits of 400 and 6100 ng/mL. The pharmacokinetics of the (+) R- and (-) S-enantiomers of ranolazine are similar in healthy volunteers. The apparent terminal half-life of ranolazine is 7 hours. Steady state is generally achieved within 3 days of twice-daily dosing with Ranexa. At steady state over the dose range of 500 to 1000 mg twice daily, Cmax and AUC0–τ increase slightly more than proportionally to dose, 2.2- and 2.4-fold, respectively. With twice-daily dosing, the trough:peak ratio of the ranolazine plasma concentration is 0.3 to 0.6. The pharmacokinetics of ranolazine is unaffected by age, gender, or food.

Absorption and Distribution

After oral administration of Ranexa, peak plasma concentrations of ranolazine are reached between 2 and 5 hours. After oral administration of ^14C-ranolazine as a solution, 73% of the dose is systemically available as ranolazine or metabolites. The bioavailability of ranolazine from Ranexa tablets relative to that from a solution of ranolazine is 76%. Because ranolazine is a substrate of P-gp, inhibitors of P-gp may increase the absorption of ranolazine.

Food (high-fat breakfast) has no important effect on the Cmax and AUC of ranolazine. Therefore, Ranexa may be taken without regard to meals. Over the concentration range of 0.25 to 10 µg/mL, ranolazine is approximately 62% bound to human plasma proteins.

Metabolism and Excretion

Ranolazine is metabolized mainly by CYP3A and, to a lesser extent, by CYP2D6. Following a single oral dose of ranolazine solution, approximately 75% of the dose is excreted in urine and 25% in feces. Ranolazine is metabolized rapidly and extensively in the liver and intestine; less than 5% is excreted unchanged in urine and feces. The pharmacologic activity of the metabolites has not been well characterized. After dosing to steady state with 500 mg to 1500 mg twice daily, the four most abundant metabolites in plasma have AUC values ranging from about 5 to 33% that of ranolazine, and display apparent half-lives ranging from 6 to 22 hours.

13 NONCLINICAL TOXICOLOGY

13.1 Carcinogenesis, Mutagenesis, Impairment of Fertility

Ranolazine tested negative for genotoxic potential in the following assays: Ames bacterial mutation assay, Saccharomyces assay for mitotic gene conversion, chromosomal aberrations assay in Chinese hamster ovary (CHO) cells, mammalian CHO/HGPRT gene mutation assay, and mouse and rat bone marrow micronucleus assays.

There was no evidence of carcinogenic potential in mice or rats. The highest oral doses used in the carcinogenicity studies were 150 mg/kg/day for 21 months in rats (900 mg/m^2/day) and 50 mg/kg/day for 24 months in mice (150 mg/m^2/day). These maximally tolerated doses are 0.8 and 0.1 times, respectively, the maximum recommended human dose (MRHD) of 2 grams on a surface area basis. A published study reported that ranolazine promoted tumor formation and progression to malignancy when given to transgenic APC (min/+) mice at a dose of 30 mg/kg twice daily [see References (15)]. The clinical significance of this finding is unclear.

13.3 Reproductive Toxicology Studies

Animal reproduction studies with ranolazine were conducted in rats and rabbits.

There was an increased incidence of misshapen sternebrae and reduced ossification of pelvic and cranial bones in fetuses of pregnant rats dosed at 400 mg/kg/day (2 times the MRHD on a surface area basis). Reduced ossification of sternebrae was observed in fetuses of pregnant rabbits dosed at 150 mg/kg/day (1.5 times the MRHD on a surface area basis). These doses in rats and rabbits were associated with an increased maternal mortality rate.

14 CLINICAL STUDIES

14.1 Chronic Stable Angina

CARISA (Combination Assessment of Ranolazine In Stable Angina) was a study in 823 chronic angina patients randomized to receive 12 weeks of treatment with twice-daily Ranexa 750 mg, 1000 mg, or placebo, who also continued on daily doses of atenolol 50 mg, amlodipine 5 mg, or diltiazem CD 180 mg. Sublingual nitrates were used in this study as needed.

In this trial, statistically significant (p < 0.05) increases in modified Bruce treadmill exercise duration and time to angina were observed for each Ranexa dose versus placebo, at both trough (12 hours after dosing) and peak (4 hours after dosing) plasma levels, with minimal effects on blood pressure and heart rate. The changes versus placebo in exercise parameters are presented in Table 1. Exercise treadmill results showed no increase in effect on exercise at the 1000 mg dose compared to the 750 mg dose.

Table 1 Exercise Treadmill Results (CARISA)
 | Mean Difference from Placebo (sec)
Study | CARISA (N = 791)
Ranexa Twice-daily Dose | 750 mg | 1000 mg
Exercise Duration
Trough | 24 [p-value ≤ 0.05] | 24
Peak | 34 [p-value ≤ 0.005] | 26
Time to Angina
Trough | 30 | 26
Peak | 38 | 38
Time to 1 mm ST-Segment Depression
Trough | 20 | 21
Peak | 41 | 35

The effects of Ranexa on angina frequency and nitroglycerin use are shown in Table 2.

Table 2 Angina Frequency and Nitroglycerin Use (CARISA)
 |  | Placebo | Ranexa 750 mg [Twice daily] | Ranexa 1000 mg
Angina Frequency (attacks/week) | N | 258 | 272 | 261
Angina Frequency (attacks/week) | Mean | 3.3 | 2.5 | 2.1
Angina Frequency (attacks/week) | p-value vs placebo | — | 0.006 | < 0.001
Nitroglycerin Use (doses/week) | N | 252 | 262 | 244
Nitroglycerin Use (doses/week) | Mean | 3.1 | 2.1 | 1.8
Nitroglycerin Use (doses/week) | p-value vs placebo | — | 0.016 | < 0.001

Tolerance to Ranexa did not develop after 12 weeks of therapy. Rebound increases in angina, as measured by exercise duration, have not been observed following abrupt discontinuation of Ranexa.

Ranexa has been evaluated in patients with chronic angina who remained symptomatic despite treatment with the maximum dose of an antianginal agent. In the ERICA (Efficacy of Ranolazine In Chronic Angina) trial, 565 patients were randomized to receive an initial dose of Ranexa 500 mg twice daily or placebo for 1 week, followed by 6 weeks of treatment with Ranexa 1000 mg twice daily or placebo, in addition to concomitant treatment with amlodipine 10 mg once daily. In addition, 45% of the study population also received long-acting nitrates. Sublingual nitrates were used as needed to treat angina episodes. Results are shown in Table 3. Statistically significant decreases in angina attack frequency (p = 0.028) and nitroglycerin use (p = 0.014) were observed with Ranexa compared to placebo. These treatment effects appeared consistent across age and use of long-acting nitrates.

Table 3 Angina Frequency and Nitroglycerin Use (ERICA)
 |  | Placebo | Ranexa [1000 mg twice daily]
Angina Frequency (attacks/week) | N | 281 | 277
Angina Frequency (attacks/week) | Mean | 4.3 | 3.3
Angina Frequency (attacks/week) | Median | 2.4 | 2.2
Nitroglycerin Use (doses/week) | N | 281 | 277
Nitroglycerin Use (doses/week) | Mean | 3.6 | 2.7
Nitroglycerin Use (doses/week) | Median | 1.7 | 1.3

Gender

Effects on angina frequency and exercise tolerance were considerably smaller in women than in men. In CARISA, the improvement in Exercise Tolerance Test (ETT) in females was about 33% of that in males at the 1000 mg twice-daily dose level. In ERICA, where the primary endpoint was angina attack frequency, the mean reduction in weekly angina attacks was 0.3 for females and 1.3 for males.

Race

There were insufficient numbers of non-Caucasian patients to allow for analyses of efficacy or safety by racial subgroup.

14.2 Lack of Benefit in Acute Coronary Syndrome

In a large (n = 6,560) placebo-controlled trial (MERLIN-TIMI 36) in patients with acute coronary syndrome, there was no benefit shown on outcome measures. However, the study is somewhat reassuring regarding proarrhythmic risks, as ventricular arrhythmias were less common on ranolazine [see Clinical Pharmacology (12.2)], and there was no difference between Ranexa and placebo in the risk of all-cause mortality (relative risk ranolazine:placebo 0.99 with an upper 95% confidence limit of 1.22).

15 REFERENCES

M.A. Suckow et al. The anti-ischemia agent ranolazine promotes the development of intestinal tumors in APC (min/+) mice. Cancer Letters 209(2004):165−9.

16 HOW SUPPLIED/STORAGE AND HANDLING

Ranexa is supplied as film-coated, oblong-shaped, extended-release tablets in the following strengths:

- 500 mg tablets are light orange, with CVT500 on one side
- 1000 mg tablets are pale yellow, with CVT1000 on one side

Ranexa (ranolazine) extended-release tablets are available in:

 | Strength | NDC
Unit-of-Use Bottle (60 Tablets) | 500 mg | 61958-1001-1
Unit-of-Use Bottle (60 Tablets) | 1000 mg | 61958-1002-1

STORAGE AND HANDLING

Store Ranexa tablets at 25 °C (77 °F) with excursions permitted to 15 ° to 30 °C (59 ° to 86 °F).

17 PATIENT COUNSELING INFORMATION

To ensure safe and effective use of Ranexa, the following information and instructions should be communicated to the patient when appropriate.

Patients should be advised:

- that Ranexa will not abate an acute angina episode
- to inform their physician of any other medications when taken concurrently with Ranexa, including over-the-counter medications
- that Ranexa may produce changes in the electrocardiogram (QTc interval prolongation)
- to inform their physician of any personal or family history of QTc prolongation, congenital long QT syndrome, or if they are receiving drugs that prolong the QTc interval such as Class Ia (e.g., quinidine) or Class III (e.g., dofetilide, sotalol, amiodarone) antiarrhythmic agents, erythromycin, and certain antipsychotics (e.g., thioridazine, ziprasidone)
- that Ranexa should not be used in patients who are receiving drugs that are strong CYP3A inhibitors (e.g., ketoconazole, clarithromycin, nefazodone, ritonavir)
- that initiation of treatment with Ranexa should be avoided during administration of inducers of CYP3A (e.g., rifampin, rifabutin, rifapentin, barbiturates, carbamazepine, phenytoin, St. John's wort)
- to inform their physician if they are receiving drugs that are moderate CYP3A inhibitors (e.g., diltiazem, verapamil, erythromycin) or P-gp inhibitors (e.g., cyclosporine)
- that grapefruit juice or grapefruit products should be limited when taking Ranexa
- that Ranexa should generally not be used in patients with clinically significant liver impairment
- that doses of Ranexa higher than 1000 mg twice daily should not be used
- that if a dose is missed, the usual dose should be taken at the next scheduled time. The next dose should not be doubled
- that Ranexa may be taken with or without meals
- that Ranexa tablets should be swallowed whole and not crushed, broken, or chewed
- to contact their physician if they experience fainting spells while taking Ranexa
- that Ranexa may cause dizziness and lightheadedness; therefore, patients should know how they react to this drug before they operate an automobile, or machinery, or engage in activities requiring mental alertness or coordination

Manufactured for:
Gilead Sciences
Foster City, CA 94404 USA

Ranexa is a registered U.S. trademark of Gilead, Palo Alto, Inc.
©2010 Gilead Sciences, Inc.

21-526-GS-008 JAN10

PRINCIPAL DISPLAY PANEL - 500 mg Label

NDC 61958-1001-1
60 tablets

Ranexa®
(ranolazine extended-
release tablets)

500 mg

Rx only

PRINCIPAL DISPLAY PANEL - 1000 mg Label

NDC 61958-1002-1
60 tablets

Ranexa®
(ranolazine extended-
release tablets)

1000 mg

Rx only